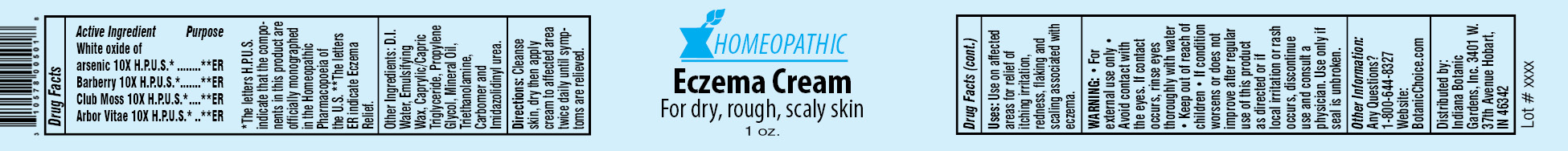 DRUG LABEL: Homeopathic Eczema
NDC: 10578-005 | Form: CREAM
Manufacturer: Indiana Botanic Gardens
Category: homeopathic | Type: HUMAN OTC DRUG LABEL
Date: 20120427

ACTIVE INGREDIENTS: ARSENIC TRIOXIDE 10 [hp_X]/28 g; BERBERIS VULGARIS ROOT BARK 10 [hp_X]/28 g; LYCOPODIUM CLAVATUM SPORE 10 [hp_X]/28 g; THUJA OCCIDENTALIS LEAFY TWIG 10 [hp_X]/28 g
INACTIVE INGREDIENTS: WATER; CETOSTEARYL ALCOHOL; POLYSORBATE 60; TRICAPRYLIN; PROPYLENE GLYCOL; MINERAL OIL; TROLAMINE; CARBOMER 934; IMIDUREA

Homeopathic Eczema Cream

Active Ingredients

White oxide of arsenic 10X H.P.U.S.*

Barberry 10X H.P.U.S.*

Club Moss 10X H.P.U.S.*

Arbor Vitae 10X H.P.U.S.*

Purpose

**ER

**ER

**ER

**ER

*The letters H.P.U.S. indicate that the components in this product are officially monographed in the Homeopathic Pharmacopoeia of the U.S. **The letters ER indicate Eczema Relief.

Other Ingredients:

D.I. Water, Emulsifying Wax, Caprylic/Capric Triglyceride, Propylene Glycol, Mineral Oil, Triethanolamine, Carbomer and Imidazolidinyl urea.

Directions:

Cleanse skin, dry then apply cream to affected area twice daily until symptoms are relieved.

Uses:

Use on affected areas for relief of itching irritation, redness, flaking and scaling associated with eczema.

WARNING:

- for external use only
- Avoid contact with the eyes. If contact occurs, rinse eyes thoroughly with water

- Keep out of reach of children

STOP USE

- If condition worsens or does not improve after regular use of this product as directed or if local irritation or rash occurs, discontinue use and consult a physician.

Use only if seal is unbroken.

Other Information:

Any Questions?

1-800-644-8327

Website:

BotanicChoice.com

Distributed by:

Indiana Botanic Gardens, Inc. 3401 W. 37th Avenue Hobart, IN 46342

Homeopathic Eczema Cream

For dry, rough, scaly skin

1 oz.